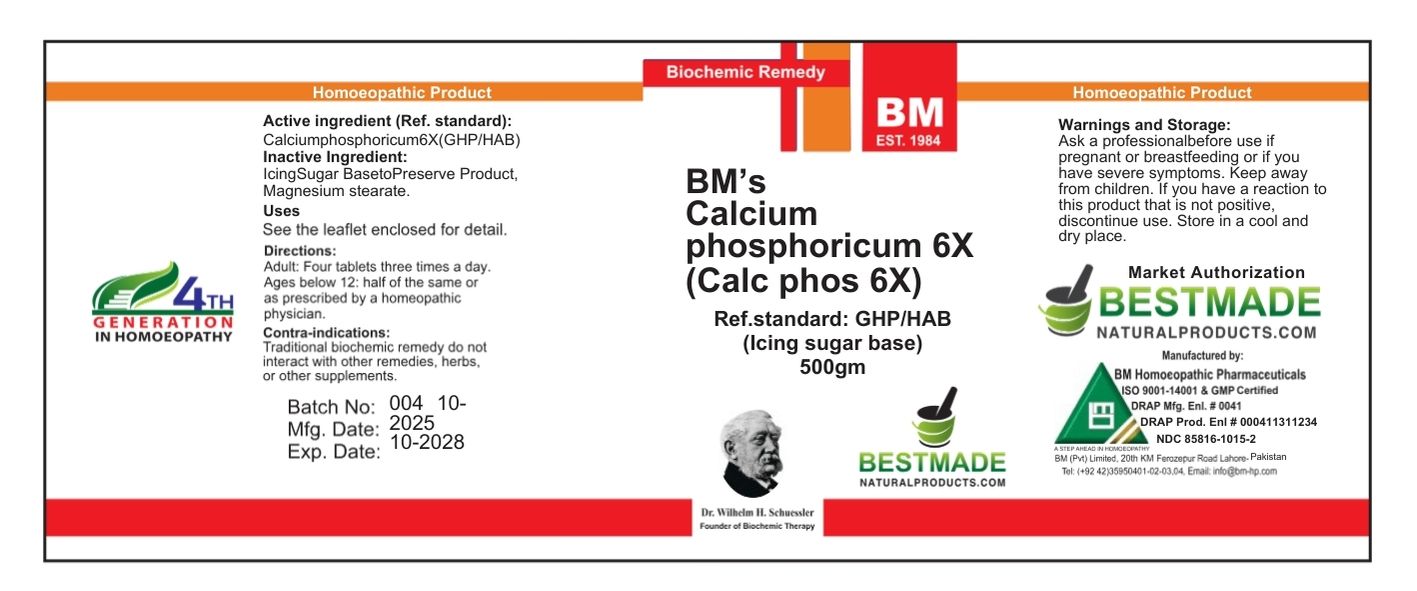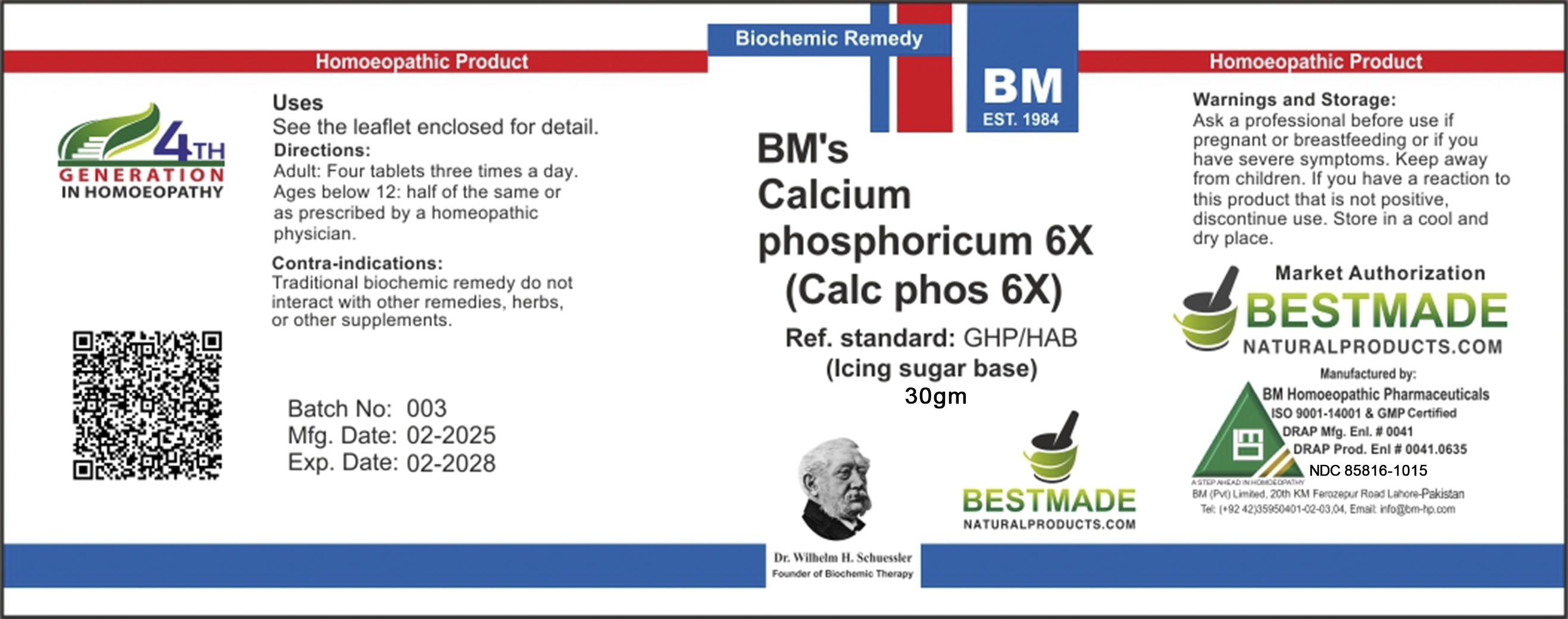 DRUG LABEL: BM Calc Phos Icing Sugar
NDC: 85816-1015 | Form: TABLET
Manufacturer: BM Private Limited
Category: homeopathic | Type: HUMAN OTC DRUG LABEL
Date: 20251202

ACTIVE INGREDIENTS: TRIBASIC CALCIUM PHOSPHATE 6 [hp_X]/60 mg
INACTIVE INGREDIENTS: SUCROSE 58.86 mg/60 mg; SILICON DIOXIDE 0.06 mg/60 mg; GELATIN, UNSPECIFIED 0.9 mg/60 mg; MAGNESIUM STEARATE 0.12 mg/60 mg

BM Calc Phos 6X Icing Sugar

Uses
See the leaflet enclosed for detail.

Uses
See the leaflet enclosed for detail.

Directions:
Adult: Four tablets three times a day.
Ages below 12: half of the same or as prescribed by a homeopathic physician.

KEEP OUT OF REACH OF CHILDREN

Warnings and Storage:

Ask a professional before use if pregnant or breastfeeding or if you have severe symptoms. Keep away from children. If you have a reaction to this product that is not positive, discontinue use. Store in a cool and dry place.

Warnings and Storage:

Ask a professional before use if pregnant or breastfeeding or if you have severe symptoms. Keep away from children. If you have a reaction to this product that is not positive, discontinue use. Store in a cool and dry place.

CONTRAINDICATIONS

Contra-indications:
Traditional biochemic remedy do not interact with other remedies, herbs, or other supplements.

Active Ingredient: Calcarea Phosphorica

INACTIVE INGREDIENT

Inactive Ingredients: Sucrose, Gelatin, Magnesium Stearate, Silicon Dioxide

Package 1 (30g)

Package 2 (500g)